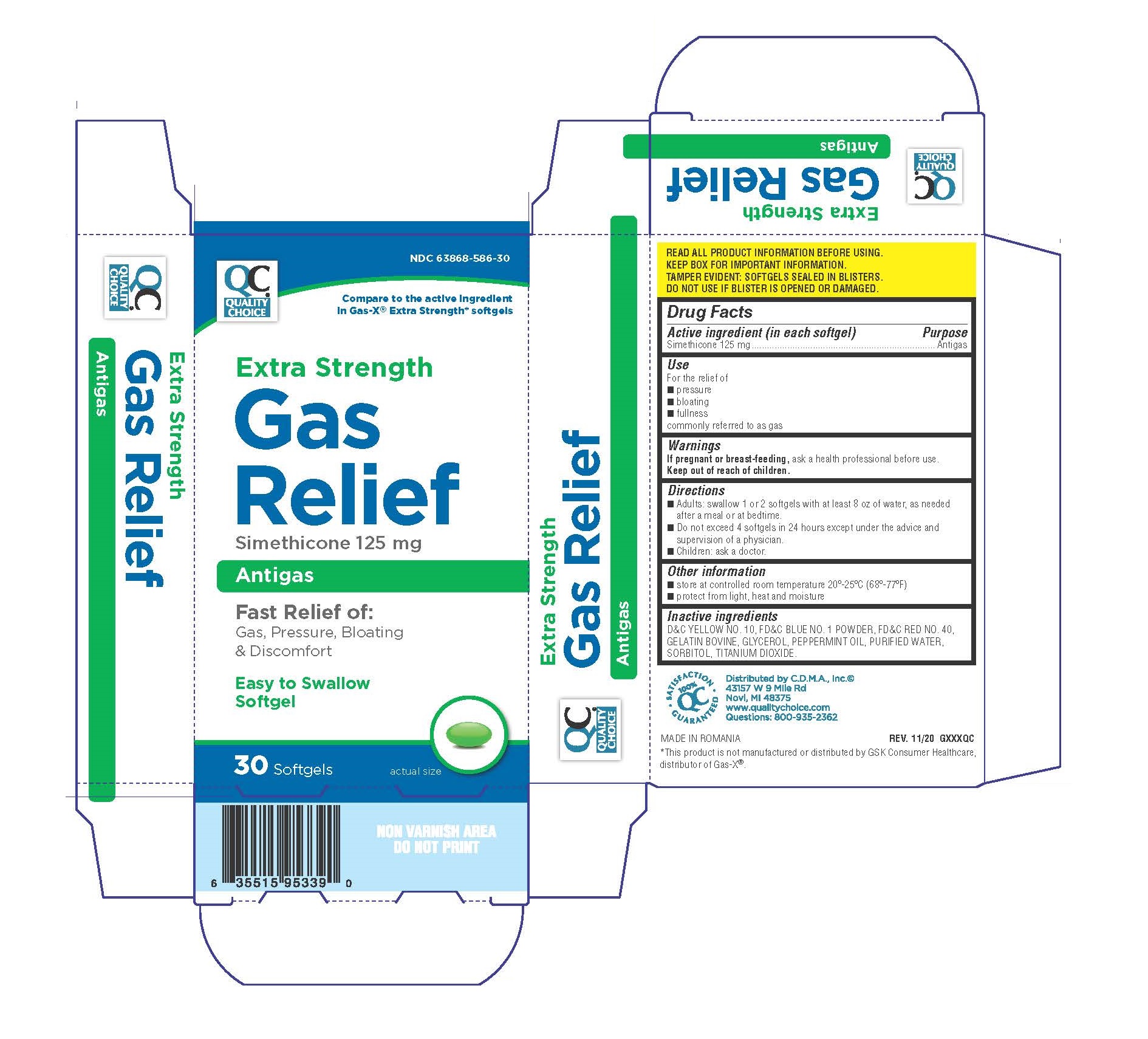 DRUG LABEL: Quality Choice Gas Relief
NDC: 83324-196 | Form: CAPSULE, LIQUID FILLED
Manufacturer: Chain Drug Marketing Association
Category: otc | Type: HUMAN OTC DRUG LABEL
Date: 20251202

ACTIVE INGREDIENTS: DIMETHICONE 125 mg/1 1
INACTIVE INGREDIENTS: D&C YELLOW NO. 10; FD&C BLUE NO. 1; FD&C RED NO. 40; GELATIN TYPE B BOVINE (230 BLOOM); GLYCERIN; PEPPERMINT OIL; TITANIUM DIOXIDE; SORBITOL

Drug Facts

Active ingredient (in each softgel)

Simethicone 125mg

Purpose

Antigas

Use

for the relief of

- pressure, bloating, and fullness commonly referred to as gas

Directions

- adults: swallow with water 1 or 2 softgels as needed after meals and at bedtime
- do not exceed 4 softgels in 24 hours except under the advice and supervision of a physician

Other information

- store at controlled room temperature 20-25ºC (68-77ºF)
- protect from light, heat, and moisture

Inactive ingredients

D&C yellow 10, FD&C blue 1, FD&C red 40, gelatin, glycerin, hypromellose, peppermint oil, sorbitan, sorbitol, titanium dioxide

Questions or comments?

800-935-2362